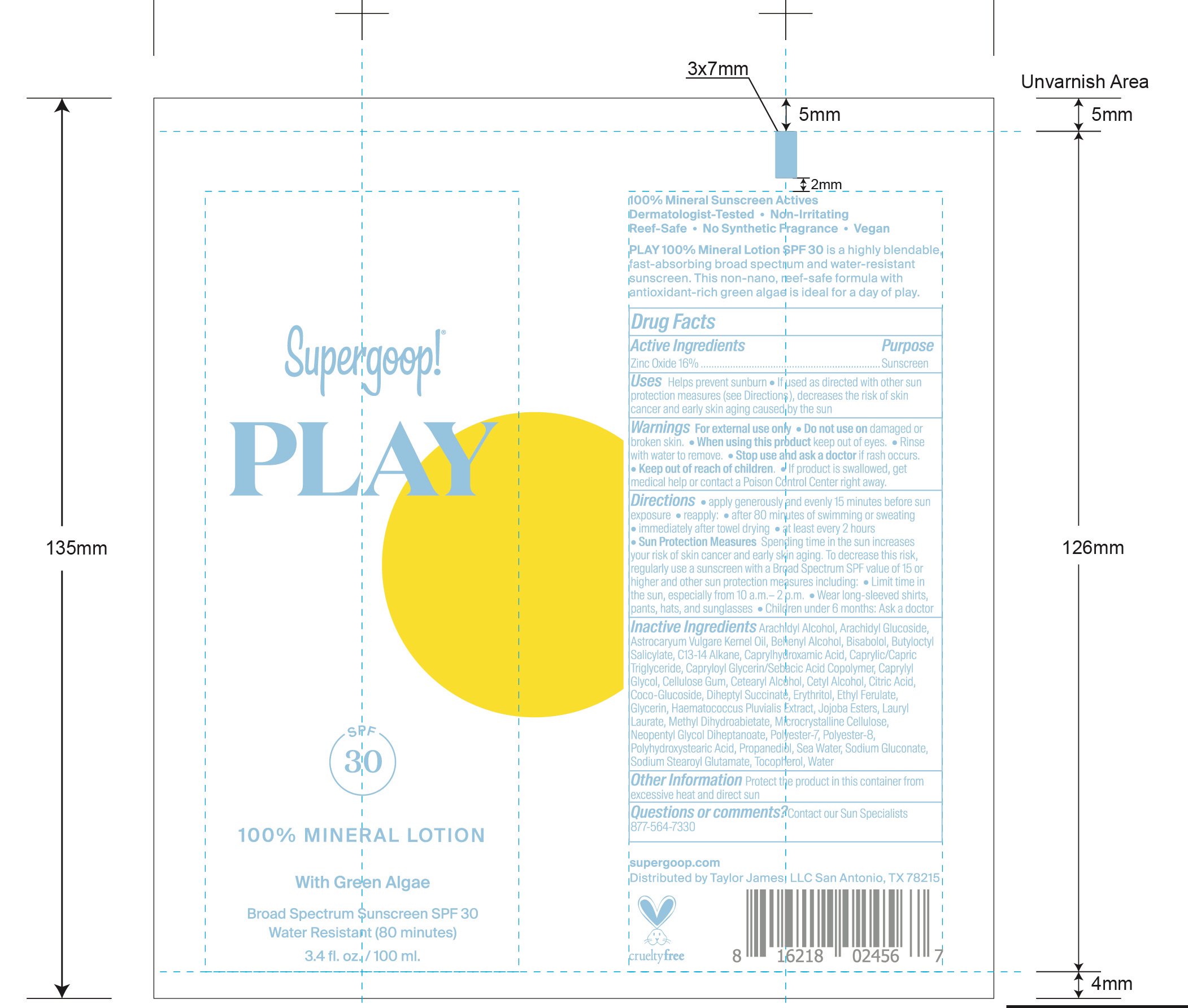 DRUG LABEL: 100% Mineral Broad Spectrum Sunscreen SPF 30
NDC: 75936-363 | Form: LOTION
Manufacturer: Supergoop LLC
Category: otc | Type: HUMAN OTC DRUG LABEL
Date: 20241218

ACTIVE INGREDIENTS: ZINC OXIDE 16 g/100 mL
INACTIVE INGREDIENTS: ARACHIDYL ALCOHOL; DOCOSANOL; BUTYLOCTYL SALICYLATE; SODIUM GLUCONATE; COCO GLUCOSIDE; ETHYL FERULATE; HAEMATOCOCCUS PLUVIALIS; METHYL DIHYDROABIETATE; MICROCRYSTALLINE CELLULOSE; NEOPENTYL GLYCOL DIHEPTANOATE; POLYESTER-7; POLYHYDROXYSTEARIC ACID (2300 MW); SODIUM STEAROYL GLUTAMATE; PROPANEDIOL; SODIUM CHLORIDE; CITRIC ACID MONOHYDRATE; WATER; TOCOPHEROL; CAPRYLOYL GLYCERIN/SEBACIC ACID COPOLYMER (2000 MPA.S); DIHEPTYL SUCCINATE; CETYL ALCOHOL; GLYCERIN; POLYESTER-8 (1400 MW, CYANODIPHENYLPROPENOYL CAPPED); MEDIUM-CHAIN TRIGLYCERIDES; ASTROCARYUM VULGARE KERNEL OIL; CAPRYLHYDROXAMIC ACID; LEVOMENOL; ERYTHRITOL; LAURYL LAURATE; CAPRYLYL GLYCOL; CARBOXYMETHYLCELLULOSE SODIUM, UNSPECIFIED; CETOSTEARYL ALCOHOL; ARACHIDYL GLUCOSIDE

100% Mineral Lotion Broad Spectrum Sunscreen SPF 30 with Green Algae

Active Ingredients Purpose

Zinc Oxide 16% Sunscreen

Uses

Helps prevent sunburn

If used as directed with other sun protection measures (see Directions), decreases the risk of skincancer and early skin aging caused by the sun

Keep out of reach of children

Stop use and ask a doctor if rash occurs.

Warnings

For external use only

- Do not use on damaged or broken skin
- When using this product keep out of eyes
- Rinse with water to remove.
- If product is swallowed, get medical help or contact a Poison Control right away.

Directions

- apply generously and evenly 15 minutes before sun exposure

reapply

- after80 minutes of swimming or sweating
- immediately after towel drying
- at least every 2 hours
- Sun Protection Measures Spending time in the sun increases your risk of skin cancer and early skin aging. To decrease this risk, regularly use a sunscreen with a Broad Spectrum SPF value of 15 or higher and other sub and other sun protection measures including:
- Limit time in the sun, especially from 10 a.m.- 2 p.m.
- Wear long-sleeved shirts, pants, hats and sunglasses
- Children under 6 months: Ask a doctor

INACTIVE INGREDIENT

Inactive Ingredients Arachidyl Alcohol, Arachidyl Glucoside, Astrocaryum Vulgare Kernel Oil, Behenyl Alcohol, Bisabolol, Butyloctyl Salicylate, C13-14 Alkane, Caprylhydroxamic Acid, Caprylic/Capric Triglyceride, Capryloyl Glycerin/Sebacic Acid Copolymer, Caprylyl Glycol, Cellulose Gum, Cetearyl Alcohol, Cetyl Alcohol, Citric Acid, Coco-Glucosde, Diheptyl Succinate, Erythritol, Ethyl Ferulate, Glycerin, Haematococcus Pluvialis Extract, Jojoba Esters, Lauryl Laurate, Methyl dihydroabietate, Microcrystalline Cellulose, Neopentyl Glycol Diheptanoate, Polyester-7, Polyester-8, Polyhydroxystearic Acid, Propanediol, Sea Water, Sodium Gluconate, Sodium Stearoyl Glutamate, Tocopherol, Water

PACKAGE LABEL

Supergoop!

PLAY

SPF 30

100% Mineral Lotion

With Green Algae

Broad Spectrum Sunscreen SPF 30

Water Resistant (80 minutes)

3.4 fl. oz. / 100 ml.